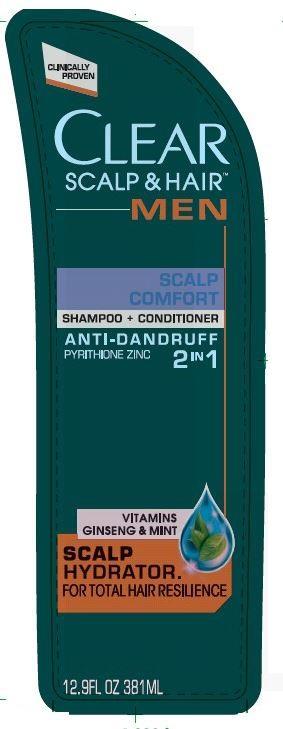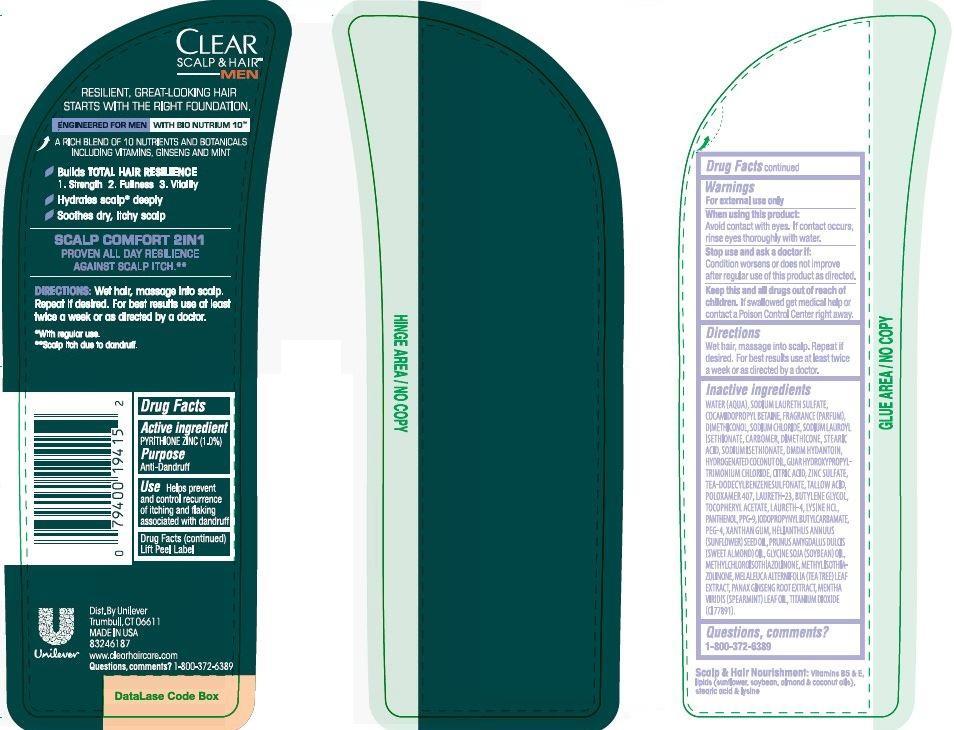 DRUG LABEL: Clear
NDC: 64942-1309 | Form: SHAMPOO
Manufacturer: Conopco Inc. d/b/a Unilever
Category: otc | Type: HUMAN OTC DRUG LABEL
Date: 20140423

ACTIVE INGREDIENTS: Pyrithione Zinc 1 g/100 mL
INACTIVE INGREDIENTS: WATER; SODIUM LAURETH SULFATE; COCAMIDOPROPYL BETAINE; SODIUM CHLORIDE; TITANIUM DIOXIDE; SODIUM LAUROYL ISETHIONATE; DMDM HYDANTOIN; TRIETHANOLAMINE DODECYLBENZENESULFONATE; SUNFLOWER OIL; CITRIC ACID MONOHYDRATE; PPG-9; METHYLCHLOROISOTHIAZOLINONE; METHYLISOTHIAZOLINONE; SPEARMINT OIL; GUAR HYDROXYPROPYLTRIMONIUM CHLORIDE (1.7 SUBSTITUENTS PER SACCHARIDE); STEARIC ACID; ZINC SULFATE; DIMETHICONOL (41 MPA.S); DIMETHICONE; SODIUM ISETHIONATE; POLOXAMER 407; LAURETH-23; LAURETH-4; .ALPHA.-TOCOPHEROL ACETATE, D-; ALMOND OIL; POLYETHYLENE GLYCOL 400000; PANTHENOL; LYSINE HYDROCHLORIDE; HYDROGENATED COCONUT OIL; SOYBEAN OIL; XANTHAN GUM; ASIAN GINSENG; TEA TREE OIL; TALLOW ACID, BEEF; BUTYLENE GLYCOL; IODOPROPYNYL BUTYLCARBAMATE

Clear 2 in 1 Scalp Comfort Anti Dandruff Shampoo and Conditioner

Active Ingredient

PYRITHIONE ZINC (1.0%)

Purpose

Anti-Dandruff

INDICATIONS AND USAGE

Use Helps prevent and control recurrence of itching and flaking associated with dandruff

Warnings
For external use only

When using this product: Avoid contact with eyes. If contact occurs, rinse eyes thoroughly with water.

Stop use and ask a doctor if: Condition worsens or does not improve after regular use of this product as directed.

KEEP OUT OF REACH OF CHILDREN

Keep this and all drugs out of reach of children. If swallowed, get medical help or contact a Poison Control Center right away.

Directions

Wet hair, massage into scalp. Repeat if desired. For best results use at least twice a week or as directed by a doctor.

Inactive Ingredients:

Questions, Comments?

1-800-372-6389